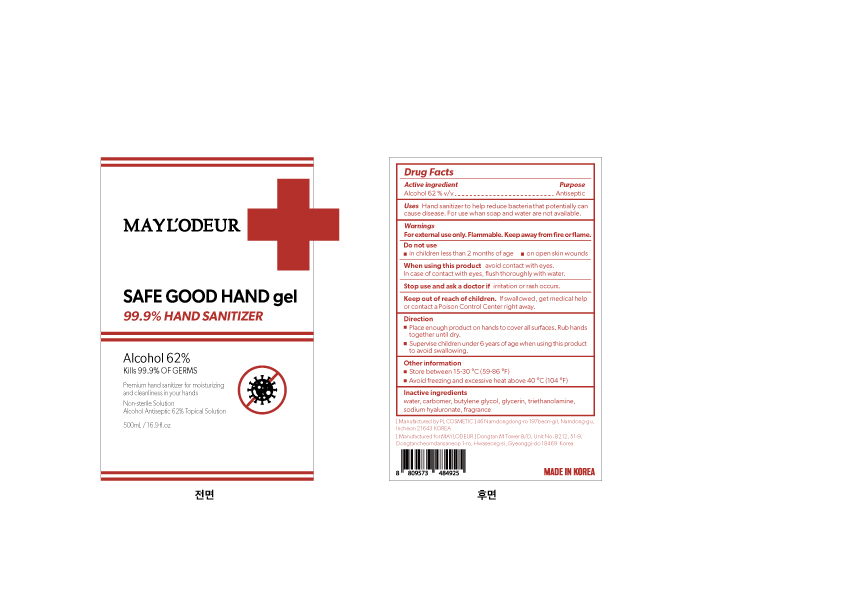 DRUG LABEL: MAYLODEUR SAFE GOOD HAND gel
NDC: 74339-1500 | Form: GEL
Manufacturer: PL COSMETIC
Category: otc | Type: HUMAN OTC DRUG LABEL
Date: 20200407

ACTIVE INGREDIENTS: ALCOHOL 310 mL/500 mL
INACTIVE INGREDIENTS: GLYCERIN; CARBOMER HOMOPOLYMER, UNSPECIFIED TYPE; WATER; BUTYLENE GLYCOL; HYALURONATE SODIUM; TROLAMINE

MAYL'ODEUR [SAFE GOOD HAND gel ] 500 ml : 74339-1500